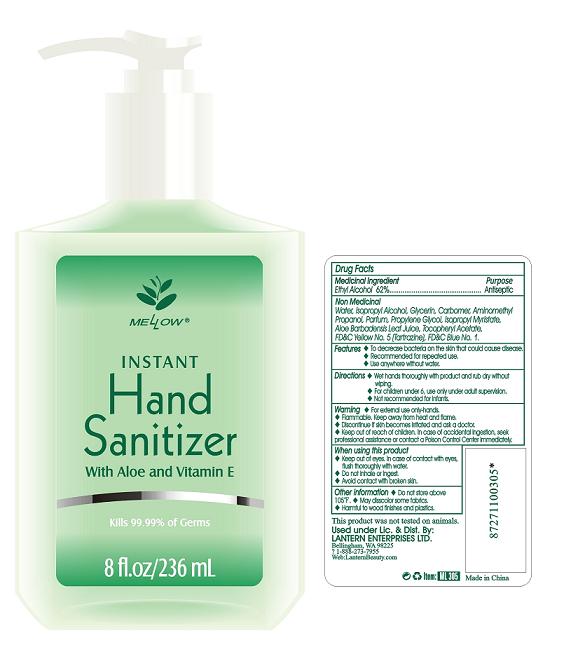 DRUG LABEL: Mellow Instant Hand Sanitizer With Aloe and Vitamin E
NDC: 50154-0030 | Form: GEL
Manufacturer: Lantern Enterprises Ltd.
Category: otc | Type: HUMAN OTC DRUG LABEL
Date: 20111012

ACTIVE INGREDIENTS: ALCOHOL 62 mL/100 mL
INACTIVE INGREDIENTS: WATER; ISOPROPYL ALCOHOL; GLYCERIN; AMINOMETHYLPROPANOL; PROPYLENE GLYCOL; ISOPROPYL MYRISTATE; ALOE VERA LEAF; .ALPHA.-TOCOPHEROL ACETATE, D-; FD&C YELLOW NO. 5; FD&C BLUE NO. 1

Instant Hand Sanitizer With Aloe and Vitamin E

Medicinal Ingredient

Ethyl Alcohol 62%

Purpose

Antiseptic

Non-Medicinal

Water, Isopropyl Alcohol, Glycerin, Carbomer, Aminomethyl Propanol, Parfum, Propylene Glycol,, Isopropyl Myristate, Aloe Barbadensis Leaf Juice, Tocopheryl Acetate, FD and C Yellow No. 5 (Tartrazine), FD and C Blue No. 1.

Features

- To decrease bacteria on the skin that could cause disease.
- Recommended for repeated use.
- Use anywhere without water.

Directions

- Wet hands thoroughly with product and rub dry without wiping.
- For children under 6, use only under adult supervision.
- Not recommended for infants.

Warning

- For external use only - hands.
- Flammable. Keep away from heat and flame.
- Discontinue if skin becomes irritated and ask a doctor.

Keep out of reach of children.

In case of accidental ingestion, seek professional assistance or contact a Poison Control Center immediately.

When using this product
- Keep out of eyes. In case of contact with eyes,
flush thoroughly with water.
- Do not inhale or ingest.
- Avoid contact with broken skin.

Other Information
- Do not store above 105 degrees F.
- May disscolor some fabrics.
- Harmful to wood finishes and plastics.

QUESTIONS

This product was not tested on animals.

Made in China

Used under Lic. and Dist. By:
LANTERN ENTERPRISES LTD.
Bellingham, WA 98225
1-888-273-7955
Web: LanternBeauty.com